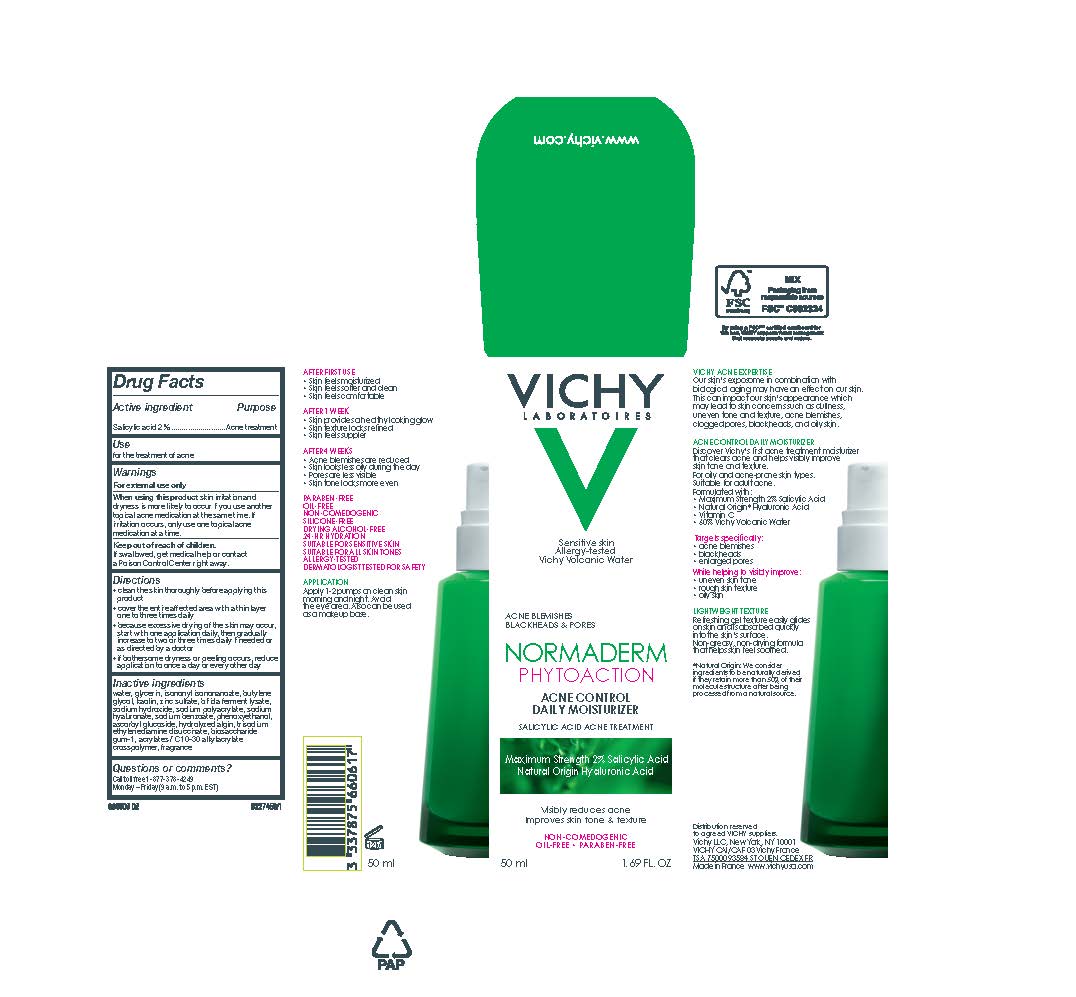 DRUG LABEL: Vichy Laboratoires Normaderm Phytoaction Acne Control Moisturizer
NDC: 69625-605 | Form: GEL
Manufacturer: COSMETIQUE ACTIVE PRODUCTION
Category: otc | Type: HUMAN OTC DRUG LABEL
Date: 20250228

ACTIVE INGREDIENTS: Salicylic Acid 20 mg/1 mL
INACTIVE INGREDIENTS: WATER; GLYCERIN; ISONONYL ISONONANOATE; BUTYLENE GLYCOL; KAOLIN; ZINC SULFATE; SODIUM HYDROXIDE; HYALURONATE SODIUM; SODIUM BENZOATE; PHENOXYETHANOL; ASCORBYL GLUCOSIDE; TRISODIUM ETHYLENEDIAMINE DISUCCINATE; BIOSACCHARIDE GUM-1; CARBOMER INTERPOLYMER TYPE A (ALLYL SUCROSE CROSSLINKED)

Drug Facts

Active ingredient

Salicylic acid...2%

Purpose

Acne treatment

Use

for the treatment of acne

Warnings

For external use only

When using this product

kin irritation and dryness is more likely to occur if you use another topical acne medication at the same time. if irritation occurs, only use one topical acne medication at a time.

Keep out of reach of children.

If swallowed, get medical help or contact a Poison Control Center right away.

Directions

• clean the skin thoroughly before applying this product
• cover the entire affected area with a thin layer one to three times daily
• because excessive drying of the skin may occur, start with one application daily, then gradually increase to two or three times daily if needed or as directed by a doctor
• if bothersome dryness or peeling occurs, reduce application to once a day or every other day

Inactive ingredients

water, glycerin, isononyl isononanoate, butylene glycol, kaolin, zinc sulfate, bifida ferment lysate, sodium hydroxide, sodium polyacrylate, sodium hyaluronate, sodium benzoate, phenoxyethanol, ascorbyl glucoside, hydrolyzed algin, trisodium ethylenediamine disuccinate, biosaccharide gum-1, acrylates/c10-30 alkyl acrylate crosspolymer, fragrance

Questions or comments?

Call toll free 1-877-378-4245

Monday - Friday (9 a.m. to 5 p.m. EST)